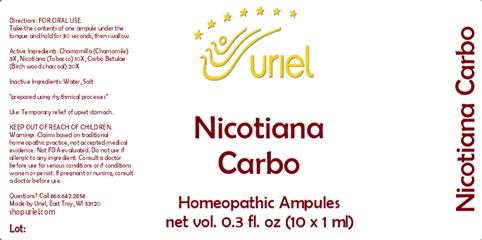 DRUG LABEL: Nicotiana Carbo
NDC: 48951-7187 | Form: LIQUID
Manufacturer: Uriel Pharmacy Inc.
Category: homeopathic | Type: HUMAN OTC DRUG LABEL
Date: 20240513

ACTIVE INGREDIENTS: MATRICARIA RECUTITA 3 [hp_X]/1 mL; TOBACCO LEAF 10 [hp_X]/1 mL; ACTIVATED CHARCOAL 20 [hp_X]/1 mL
INACTIVE INGREDIENTS: WATER; SODIUM CHLORIDE

Nicotiana Carbo

INDICATIONS AND USAGE

Directions: FOR ORAL USE.

DOSAGE AND ADMINISTRATION

Take the contents of one ampule under the tongue and hold for 30 seconds, then swallow.

ACTIVE INGREDIENT

Active Ingredients: Chamomilla (Chamomile) 3X, Nicotiana (Tobacco) 10X, Carbo Betulae (Birch wood charcoal) 20X

Inactive Ingredients: Water, Salt

"prepared using rhythmical processes"

PURPOSE

Use: Temporary relief of upset stomach.

KEEP OUT OF REACH OF CHILDREN.

WARNINGS

Warnings: Claims based on traditional homeopathic practice, not accepted medical evidence. Not FDA evaluated. Do not use if allergic to any ingredient. Consult a doctor before use for serious conditions or if conditions worsen or persist. If pregnant or nursing, consult a doctor before use.

QUESTIONS

Questions? Call 866.642.2858 Made by Uriel, East Troy, WI 53120 shopuriel.com Lot: